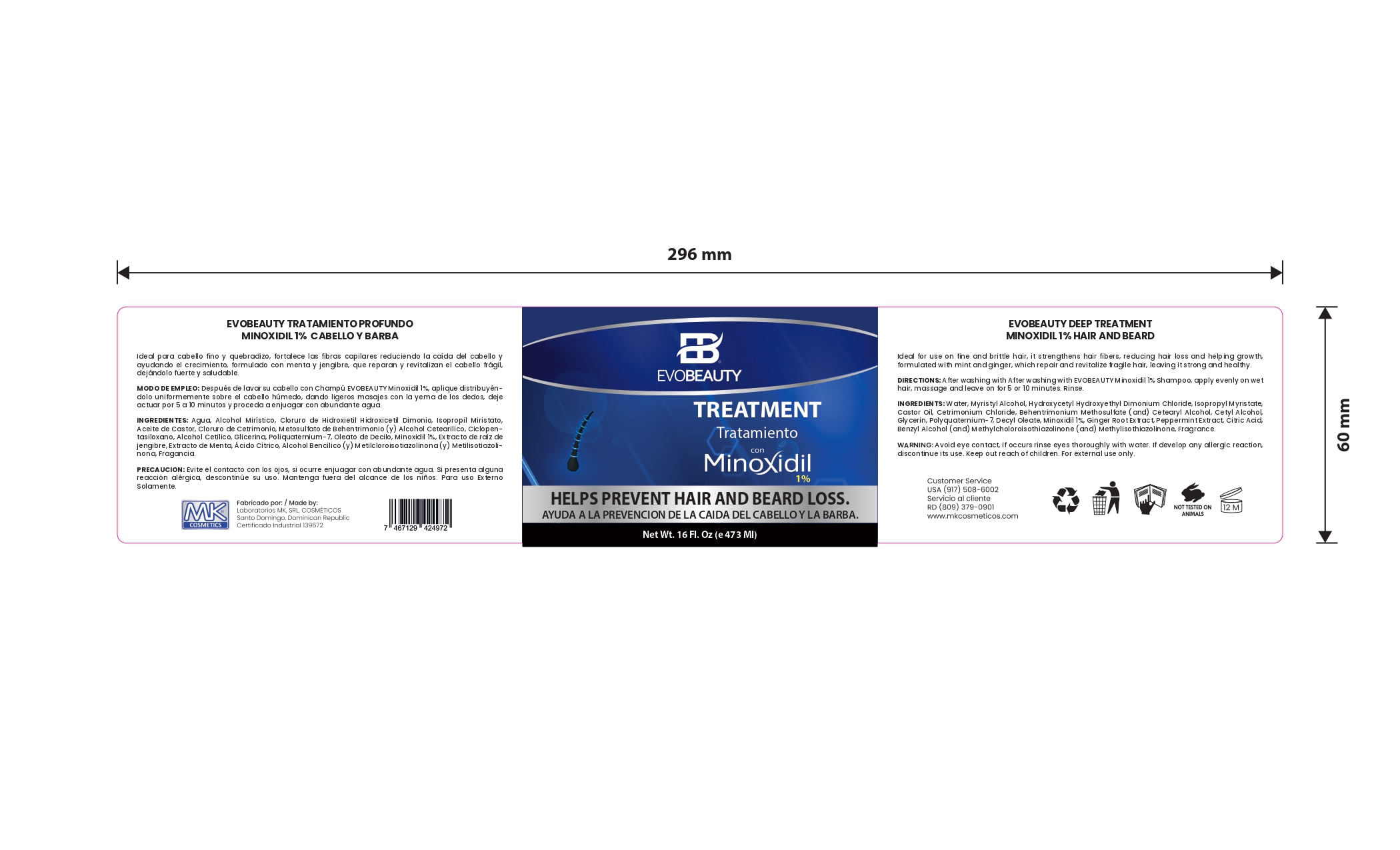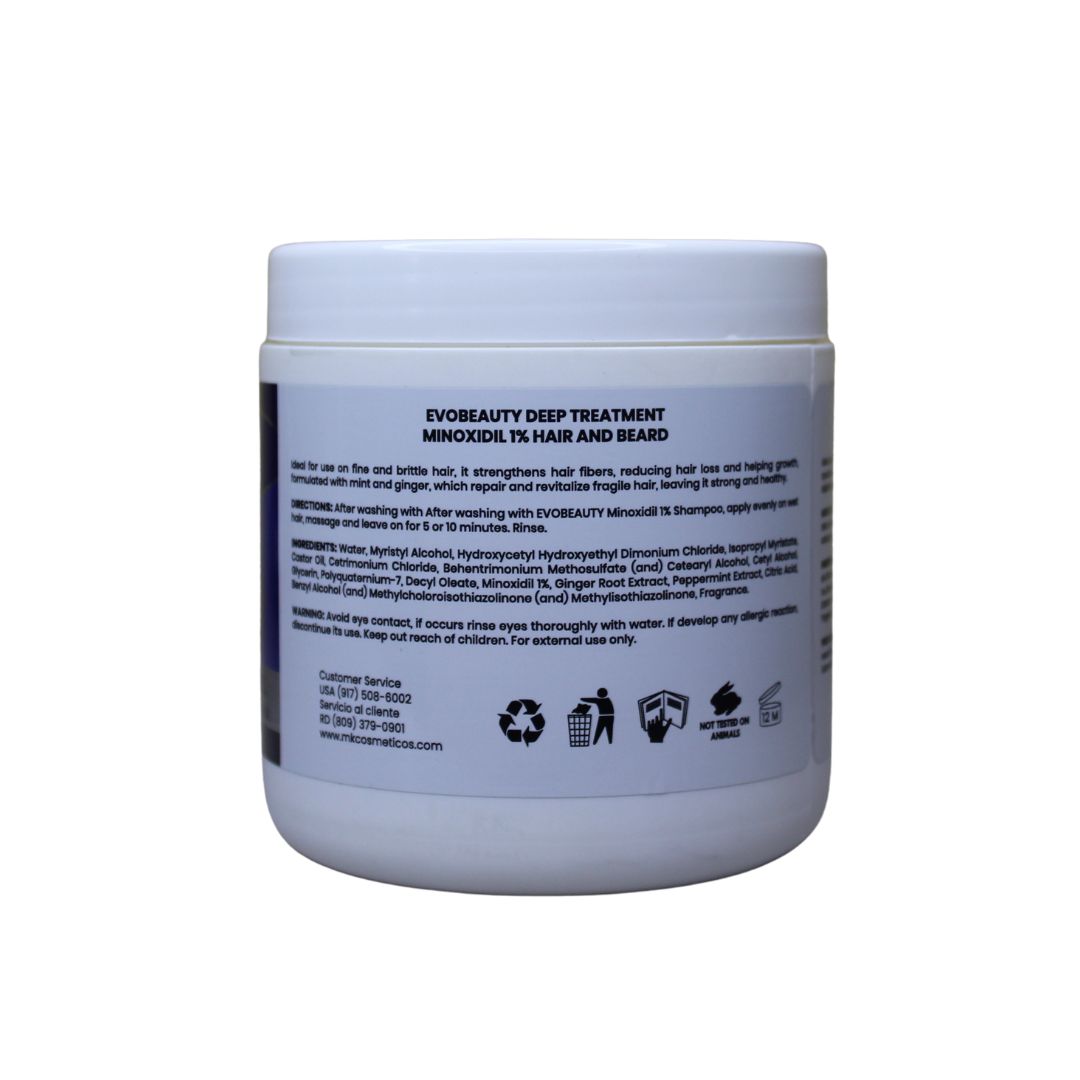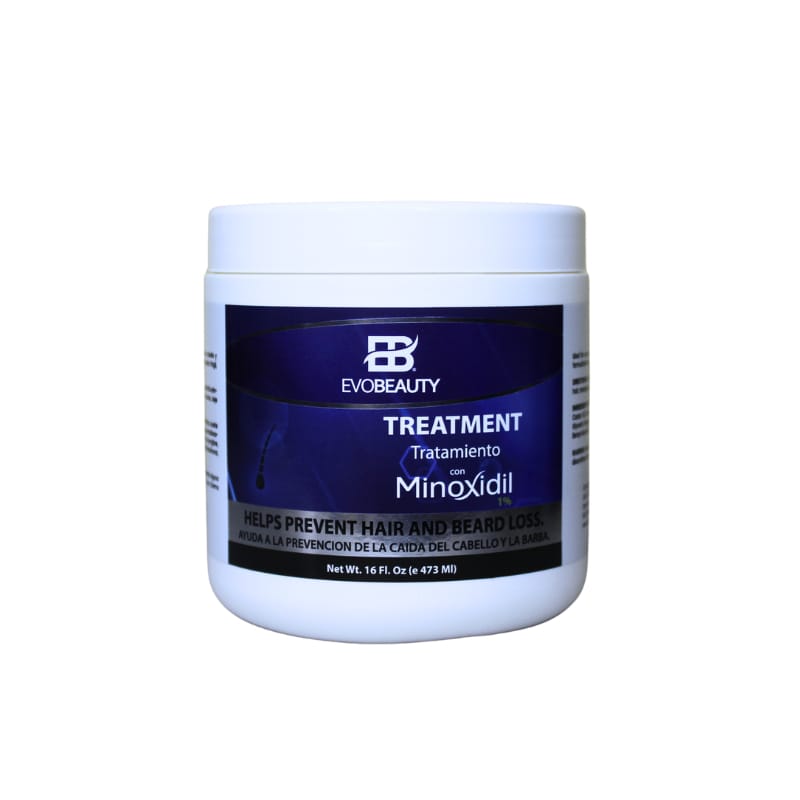 DRUG LABEL: hair treatment
NDC: 87022-009 | Form: CREAM
Manufacturer: LABORATORIO MK SRL
Category: otc | Type: HUMAN OTC DRUG LABEL
Date: 20250829

ACTIVE INGREDIENTS: MINOXIDIL 1 mg/473 mL
INACTIVE INGREDIENTS: HYDROXYCETYL HYDROXYETHYL DIMONIUM CHLORIDE; WATER; CETEARYL ALCOHOL; CETYL ALCOHOL; ISOPROPYL MYRISTATE; BEHENTRIMONIUM METHOSULFATE; PEPPERMINT; .ALPHA.,.ALPHA.-DIMETHYLBENZYL ALCOHOL; CETRIMONIUM CHLORIDE; METHYLISOTHIAZOLINONE; CASTOR OIL; POLYQUATERNIUM-7; DECYL OLEATE; CITRIC ACID; GLYCERIN; GINGER; METHYLCHLOROISOTHIAZOLINONE

INDICATIONS AND USAGE

After washing the hair with EVOBEAUTY Minoxidil 1% Shampoo, apply evenly on wet hair, massage and leave on for 5 or 10 minutes. Rinse.

INACTIVE INGREDIENT

Water, Myristyl Alcohol, Hydroxycetyl Hydroxyethyl Dimonium Chloride, Isopropyl Myristate, Castor Oil, Cetrimonium Chloride, Behentrimonium Methosulfate (and) Cetearyl Alcohol, Cetyl Alcohol, Glycerin, Polyquaternium-7, Decyl Oleate, Ginger Root Extract, Peppermint Extract, Citric Acid, Benzyl Alcohol (and) Methylchloroisothiazolinone (and) Methylisothiazolinone

WARNINGS

Avoid eye contact, if occurs rinse eyes thoroughly with water. If develop any allergic reaction, discontinue its use.

INFORMATION FOR OWNERS/CAREGIVERS

Customer Service USA (917)508-6002

Customer Service RD (809)379-0900

www.mkcosmeticos.com

DOSAGE AND ADMINISTRATION

After washing the hair with EVOBEAUTY Minoxidil 1% Shampoo, apply evenly on wet hair, massage and leave on for 5 or 10 minutes. Rinse.

KEEP OUT OF REACH OF CHILDREN

Keep out reach of children. For external use only.

PURPOSE

growth and help prevent hair and beard loss. Revitalizes hair follicles and stimulates growth.

PACKAGE LABEL

This is the principal panel display side of the minoxidil hair cream 1%